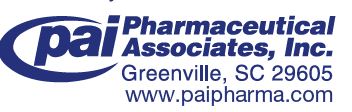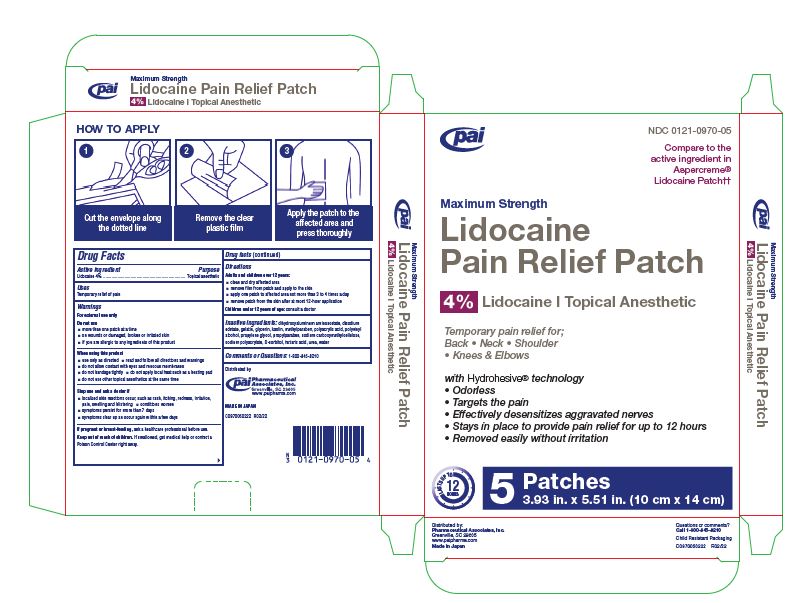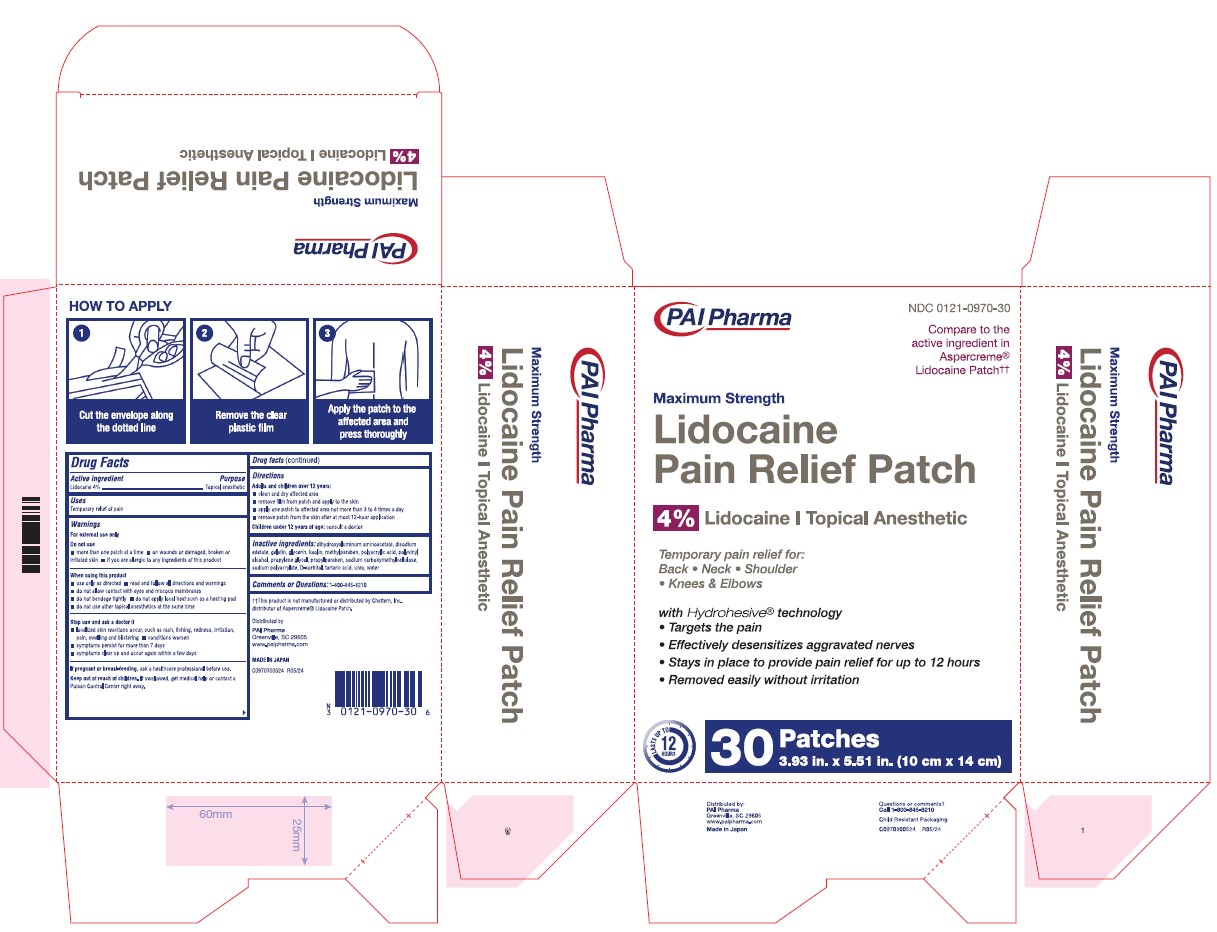 DRUG LABEL: Lidocaine Pain Relief
NDC: 0121-0970 | Form: PATCH
Manufacturer: PAI Holdings, LLC dba PAI Pharma
Category: otc | Type: HUMAN OTC DRUG LABEL
Date: 20260226

ACTIVE INGREDIENTS: LIDOCAINE 560 mg/1 1
INACTIVE INGREDIENTS: DIHYDROXYALUMINUM AMINOACETATE; EDETATE DISODIUM; GELATIN; GLYCERIN; KAOLIN; METHYLPARABEN; POLYACRYLIC ACID (250000 MW); POLYVINYL ALCOHOL (100000 MW); PROPYLENE GLYCOL; PROPYLPARABEN; CARBOXYMETHYLCELLULOSE SODIUM, UNSPECIFIED; SODIUM POLYACRYLATE (2500000 MW); SORBITOL; TARTARIC ACID; UREA; WATER

Maximum Strength
Lidocaine Pain Relief Patch
4% Lidocaine ι Topical Anesthetic

Active ingredient(s)

Lidocaine 4%

Purpose

Topical anesthetic

Uses

Temporary relief of pain

Warnings

Do not use

- more than one patch at a time
- on wounds or damaged, broken or irritated skin
- if you are allergic to any ingredients of this product

When using this product

- use only as directed • read and follow all directions and warnings

- do not allow contact with eyes and mucous membranes

- do not bandage tightly • do not apply local heat such as a heating pad

- do not use other topical anesthetics at the same time

Stop use and ask a doctor if

- localized skin reactions occur, such as rash, itching, redness, irritation,
  pain, swelling and blistering
- conditions worsen
- symptoms persist for more than 7 days
- symptoms clear up and occur again within a few days

if pregnant or breast-feeding,

ask a healthcare professional before use.

Keep out of reach of children

If swallowed, get medical help or contact a Poison Control Center right away.

Directions

Adults and children over 12 years:

- clean and dry affected area
- remove film from patch and apply to the skin
- apply one patch to affected area not more than 3 to 4 times a day
- remove patch from the skin after at most 12-hour application

Children under 12 years of age: consult a doctor

Inactive ingredients

dihydroxyaluminum aminoacetate, disodium edetate, gelatin, glycerin, kaolin, methylparaben, polyacrylic acid, polyvinyl
alcohol, propylene glycol, propylparaben, sodium carboxymethylcellulose, sodium polyacrylate, D-sorbitol, tartaric acid, urea, water

Comments or Questions:

1-800-845-8210

††This product is not manufactured or distributed by Chattem, Inc., distributor of Aspercreme® Lidocaine Patch.

Distributed by

MADE IN JAPAN

C09750050222 R02/22

Principal Display Panel

lidocaine patch

Principal Display Panel - 30 patches

NDC 0121-0970-30

Lidocaine Pain Relief Patch

4% Lidocaine / Topical Anesthetic